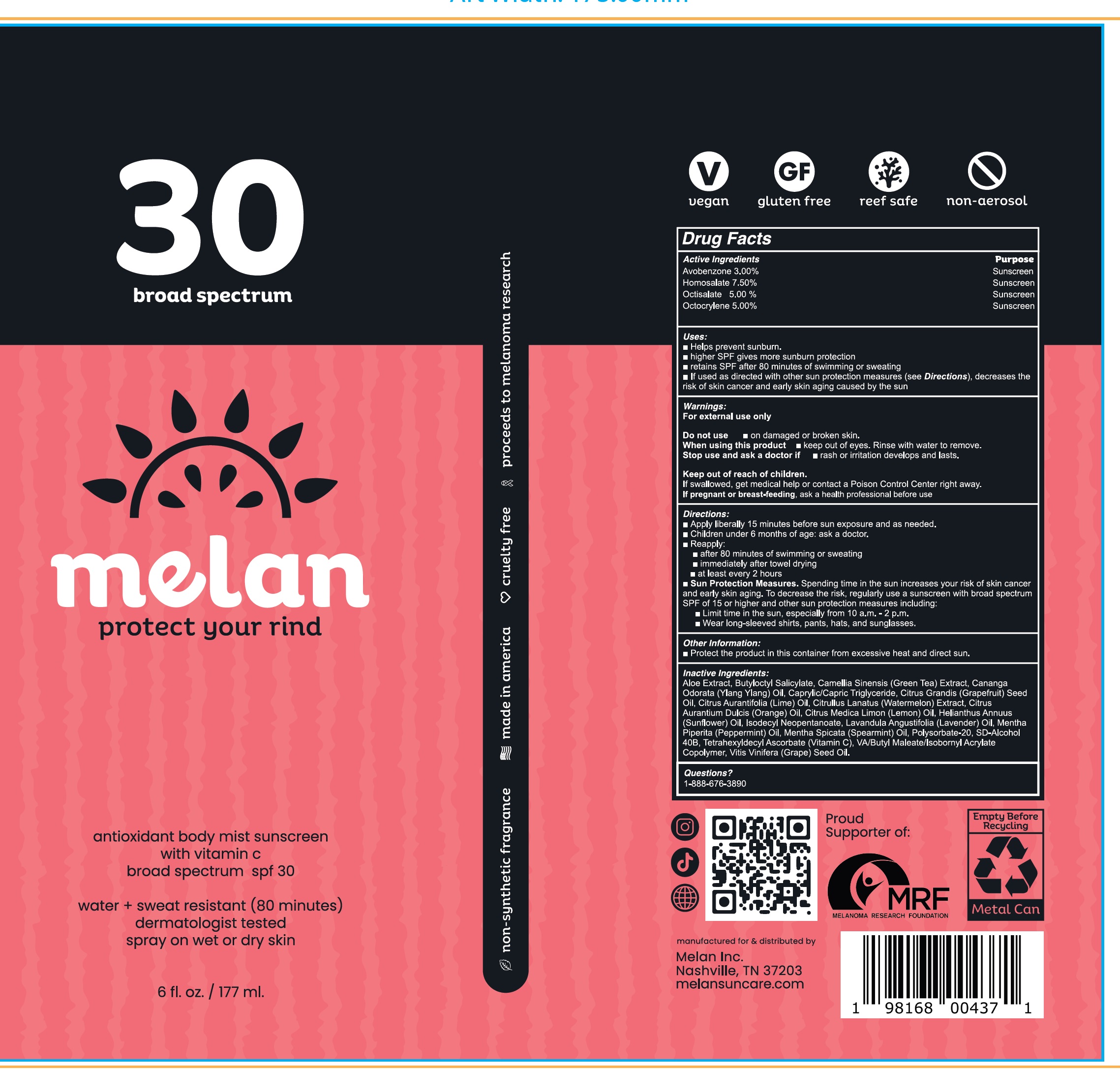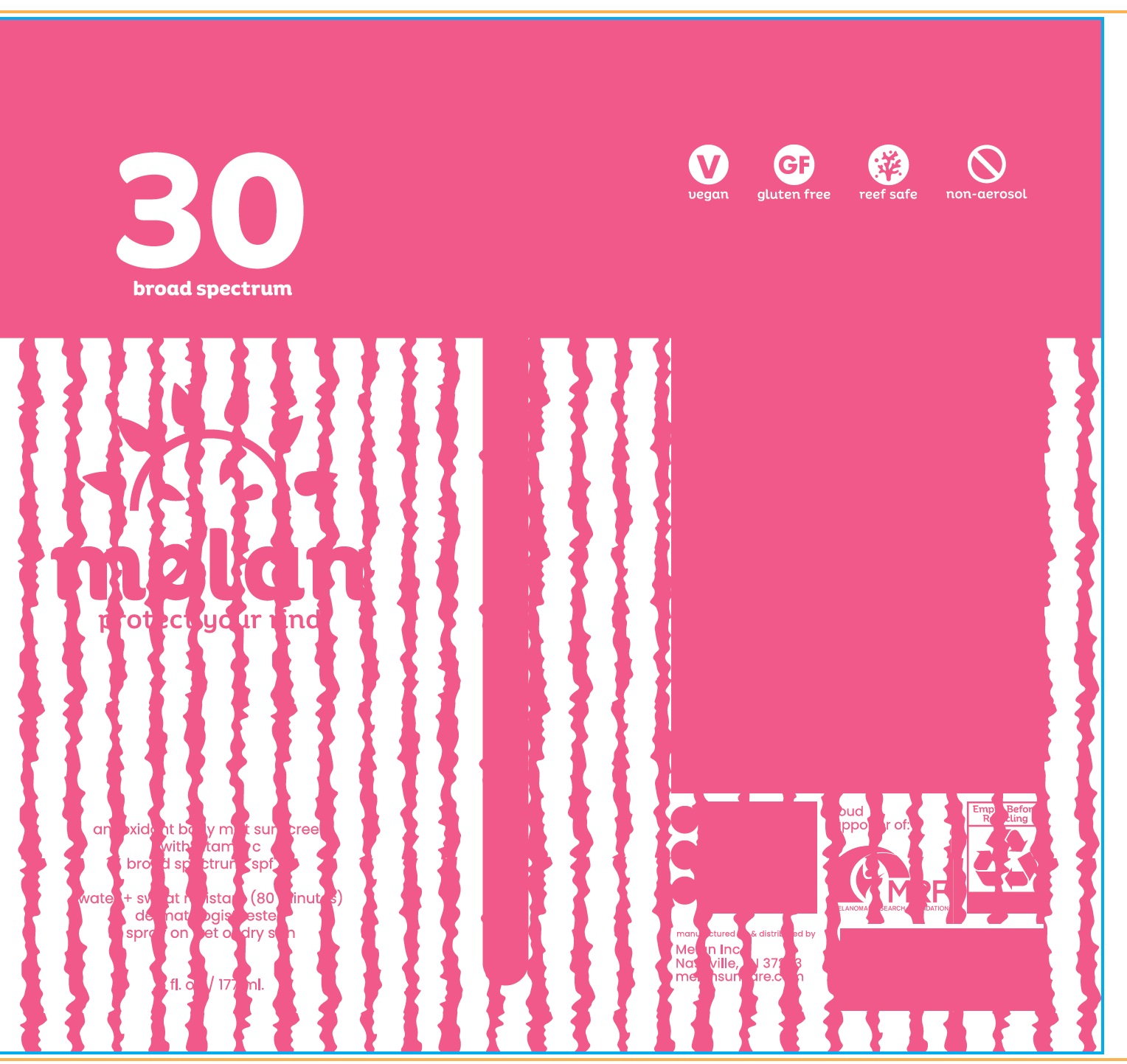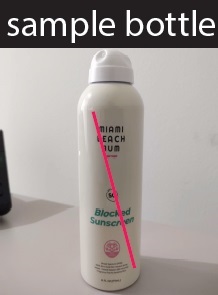 DRUG LABEL: MELAN SPF-30 Antioxidant Body Mist Sunscreen
NDC: 84294-479 | Form: LIQUID
Manufacturer: MELAN INC.
Category: otc | Type: HUMAN OTC DRUG LABEL
Date: 20240502

ACTIVE INGREDIENTS: AVOBENZONE 30 mg/1 mL; HOMOSALATE 75 mg/1 mL; OCTISALATE 50 mg/1 mL; OCTOCRYLENE 50 mg/1 mL
INACTIVE INGREDIENTS: ALOE; BUTYLOCTYL SALICYLATE; GREEN TEA LEAF; MEDIUM-CHAIN TRIGLYCERIDES; CITRUS MAXIMA SEED OIL; LIME OIL, COLD PRESSED; WATERMELON; ORANGE OIL, COLD PRESSED; LEMON; HELIANTHUS ANNUUS FLOWERING TOP; ISODECYL NEOPENTANOATE; LAVENDER OIL; PEPPERMINT OIL; SPEARMINT OIL; POLYSORBATE 20; TETRAHEXYLDECYL ASCORBATE; GRAPE SEED OIL

MELAN SPF-30 Antioxidant Body Mist Sunscreen

Active Ingredients

Avobenzone 3.00%

Homosalate 7.50%

Octisalate 5.00%

Octocrylene 5.00%

Purpose

Sunscreen

Uses:

- Helps prevent sunburn.
- higher SPF gives more sunburn protection
- retains SPF after 80 minutes of swimming or sweating
- If used as directed with other sun protection measures (see Directions), decreases the risk of skin cancer and early skin aging caused by the sun

Warnings:

For external use only

Do not use

- on damaged or broken skin.

When using this product

- keep out of eyes. Rinse with water to remove.

Stop use and ask a doctor if

- rash or irritation develops and lasts.

Keep out of reach of children.

If swallowed, get medical help or contact a Poison Control Center right away.

If pregnant or breast-feeding,

ask a health professional before use

Directions:

- Apply liberally 15 minutes before sun exposure and as needed.
- Children under 6 months of age: ask a doctor.
- Reapply:
- after 80 minutes of swimming or sweating
- immediately after towel drying
- at least every 2 hours
- Sun Protection Measures. Spending time in the sun increases your risk of skin cancer and early skin aging. To decrease the risk, regularly use a sunscreen with broad spectrum SPF of 15 or higher and other sun protection measures including:
- Limit time in the sun, especially from 10 a.m. - 2 p.m.
- Wear long-sleeved shirts, pants, hats, and sunglasses.

Other Information:

- Protect the product in this container from excessive heat and direct sun.

Inactive Ingredients:

Aloe Extract, Butyloctyl Salicylate, Camellia Sinensis (Green Tea) Extract, Cananga Odorata (Ylang Ylang) Oil, Caprylic/Capric Triglyceride, Citrus Grandis (Grapefruit) Seed Oil, Citrus Aurantifolia (Lime) Oil, Citrullus Lanatus (Watermelon) Extract, Citrus Aurantium Dulcis (Orange) Oil, Citrus Medica Limon (Lemon) Oil, Helianthus Annuus (Sunflower) Oil, Isodecyl Neopentanoate, Lavandula Angustifolia (Lavender) Oil, Mentha Piperita (Peppermint) Oil, Mentha Spicata (Spearmint) Oil, Polysorbate-20, SD-Alcohol 40B, Tetrahexyldecyl Ascorbate (Vitamin C), VA/Butyl Maleate/Isobornyl Acrylate Copolymer, Vitis Vinifera (Grape) Seed Oil.

Questions?

1-888-676-3890